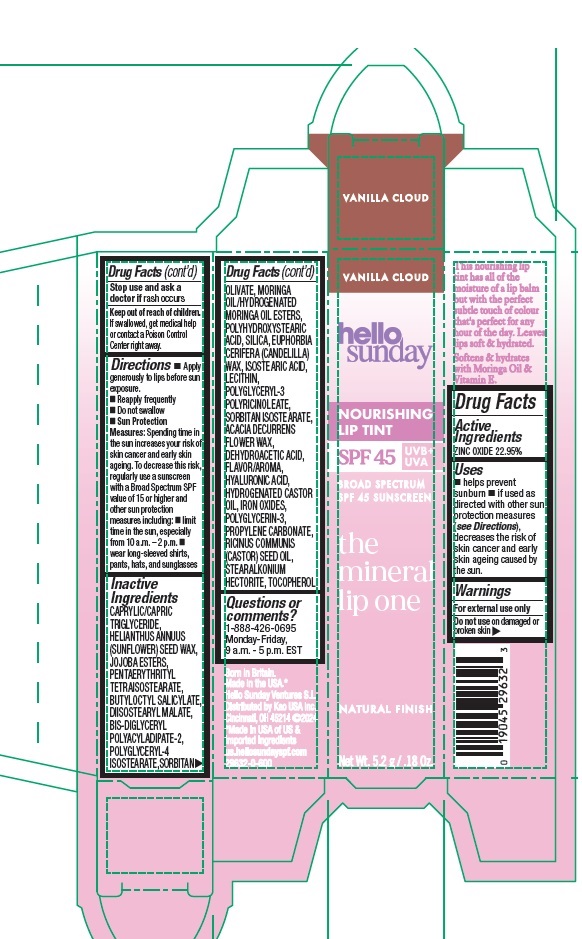 DRUG LABEL: HELLO SUNDAY THE MINERAL LIP ONE NOURISHING LIP TINT SPF 45 VANILLA CLOUD
NDC: 10596-002 | Form: STICK
Manufacturer: Kao USA Inc.
Category: otc | Type: HUMAN OTC DRUG LABEL
Date: 20260105

ACTIVE INGREDIENTS: ZINC OXIDE 229.5 mg/1 g
INACTIVE INGREDIENTS: POLYGLYCERYL-3 PENTARICINOLEATE; ACACIA DECURRENS FLOWER WAX; HYALURONIC ACID; FERRIC OXIDE RED; PROPYLENE CARBONATE; CASTOR OIL; HELIANTHUS ANNUUS (SUNFLOWER) SEED WAX; JOJOBA OIL, RANDOMIZED; SORBITAN OLIVATE; SILICON DIOXIDE; DEHYDROACETIC ACID; DIISOSTEARYL MALATE; SORBITAN ISOSTEARATE; STEARALKONIUM HECTORITE; POLYGLYCERYL-4 ISOSTEARATE; ISOSTEARIC ACID; PENTAERYTHRITYL TETRAISOSTEARATE; POLYHYDROXYSTEARIC ACID (2300 MW); BIS-DIGLYCERYL POLYACYLADIPATE-2; TOCOPHEROL; BUTYLOCTYL SALICYLATE; CANDELILLA WAX; LECITHIN, SUNFLOWER; HYDROGENATED CASTOR OIL; POLYGLYCERIN-3; CAPRYLIC/CAPRIC TRIGLYCERIDE

HELLO SUNDAY THE MINERAL LIP ONE NOURISHING LIP TINT SPF 45 VANILLA CLOUD

Active Ingredients

ZINC OXIDE 22.95%

Purpose

Sunscreen

Uses

- helps prevent sunburn
- if used as directed with other sun protection measures (see Directions), decreases the risk of skin cancer and early skin ageing caused by the sun.

Warnings

For external use only

Do not use

on damaged or broken skin

Stop use and ask a doctor if

rash occurs

Keep out of reach of children.

If swallowed, get medical help or contact a Poison Control Center right away.

Directions

- Apply generously to lips before sun exposure.
- Reapply frequently
- Do not swallow
- Sun Protection Measures: Spending time in the sun increases your risk of skin cancer and early skin ageing. To decrease this risk, regularly use a sunscreen with a Broad Spectrum SPF value of 15 or higher and other sun protection measures including:
- limit time in the sun, especially from 10 a.m. - 2 p.m.
- wear long-sleeved shirts, pants, hats, and sunglasses

Inactive Ingredients

CAPRYLIC/CAPRIC TRIGLYCERIDE, HELIANTHUS ANNUUS (SUNFLOWER) SEED WAX, JOJOBA ESTERS, PENTAERYTHRITYL TETRAISOSTEARATE, DIISOSTEARYL MALATE, BUTYLOCTYL SALICYLATE, BIS-DIGLYCERYL POLYACYLADIPATE-2, POLYGLYCERYL-4 ISOSTEARATE, SORBITAN OLIVATE, MORINGA OIL/HYDROGENATED MORINGA OIL ESTERS, POLYHYDROXYSTEARIC ACID, SILICA, EUPHORBIA CERIFERA (CANDELILLA) WAX, ISOSTEARIC ACID, LECITHIN, POLYGLYCERYL-3 POLYRICINOLEATE, SORBITAN ISOSTEARATE, ACACIA DECURRENS FLOWER WAX, DEHYDROACETIC ACID, FLAVOR/AROMA, HYALURONIC ACID, HYDROGENATED CASTOR OIL, IRON OXIDES, POLYGLYCERIN-3, PROPYLENE CARBONATE, RICINUS COMMUNIS (CASTOR) SEED OIL, STEARALKONIUM HECTORITE, TOCOPHEROL

Questions or comments?

1-888-426-0695

Monday-Friday, 9 a.m. - 5 p.m. EST